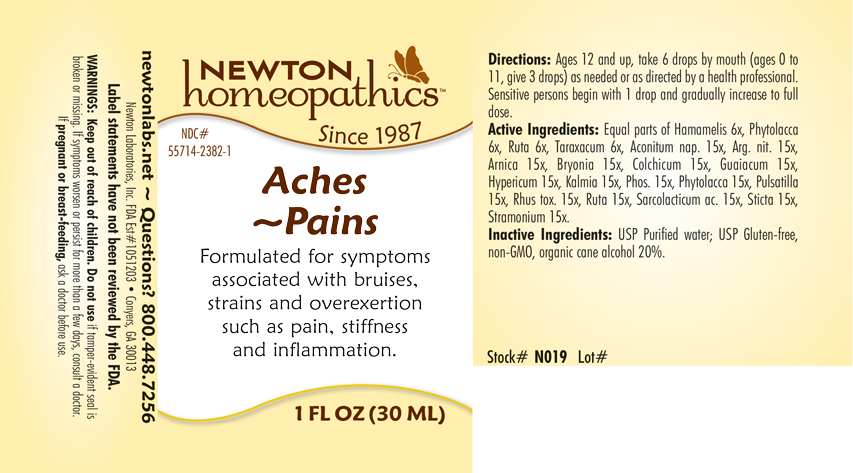 DRUG LABEL: Aches - Pains
NDC: 55714-2382 | Form: LIQUID
Manufacturer: Newton Laboratories, Inc.
Category: homeopathic | Type: HUMAN OTC DRUG LABEL
Date: 20201124

ACTIVE INGREDIENTS: ACONITUM NAPELLUS 15 [hp_X]/1 mL; SILVER NITRATE 15 [hp_X]/1 mL; ARNICA MONTANA 15 [hp_X]/1 mL; BRYONIA ALBA ROOT 15 [hp_X]/1 mL; COLCHICUM AUTUMNALE BULB 15 [hp_X]/1 mL; GUAIAC 15 [hp_X]/1 mL; HYPERICUM PERFORATUM 15 [hp_X]/1 mL; KALMIA LATIFOLIA LEAF 15 [hp_X]/1 mL; PHOSPHORUS 15 [hp_X]/1 mL; PHYTOLACCA AMERICANA ROOT 15 [hp_X]/1 mL; PULSATILLA VULGARIS 15 [hp_X]/1 mL; TOXICODENDRON PUBESCENS LEAF 15 [hp_X]/1 mL; RUTA GRAVEOLENS FLOWERING TOP 15 [hp_X]/1 mL; LACTIC ACID, L- 15 [hp_X]/1 mL; LOBARIA PULMONARIA 15 [hp_X]/1 mL; DATURA STRAMONIUM 15 [hp_X]/1 mL; HAMAMELIS VIRGINIANA ROOT BARK/STEM BARK 6 [hp_X]/1 mL; TARAXACUM OFFICINALE 6 [hp_X]/1 mL
INACTIVE INGREDIENTS: ALCOHOL; WATER

Aches - Pains 2382L

WARNINGS SECTION

Warnings: Keep our of reach of children. Do not use if tamper-evident seal is broken or missing. If symptoms worsen or persist for more than a few days, consult a doctor. If pregnant or breast-feeding, ask a doctor before use.

DOSAGE & ADMINISTRATION SECTION

Directions: Ages 12 and up, take 6 drops by mouth (ages 0 to 11, give 3 drops) as needed or as directed by a health professional. Sensitive persons begin with 1 drop and gradually increase to full dose.

OTC - KEEP OUT OF REACH OF CHILDREN SECTION

Keep out of reach of children.

OTC - PREGNANCY OR BREAST FEEDING SECTION

If pregnant or breast-feeding, ask a doctor before use.

OTC - QUESTIONS SECTION

newtonlabs.net ~ Questions? 800-448-7256

Newton Laboratories, Inc. FDA Est # 1051203 - Conyers, GA 30013

INACTIVE INGREDIENT SECTION

Inactive Ingredients: USP Purified Water; USP Gluten-free, non-GMO, organic cane dispensing alcohol 20%.

OTC - PURPOSE SECTION

Formulated for symptoms associated with bruises, strains and overexertion such as pain, stiffness and inflammation.

OTC - ACTIVE INGREDIENT SECTION

Active Ingredients: Equal parts of Hamamelis 6x, Phytolacca 6x, Ruta 6x, Taraxacum 6x, Aconitum nap. 15x, Arg. nit. 15x, Arnica 15x, Bryonia 15x, Colchicum 15x, Guaiacum 15x, Hypericum 15x, Kalmia 15x, Phos. 15x, Phytolacca 15x, Pulsatilla 15x, Rhus tox. 15x, Ruta 15x, Sarcolacticum ac. 15x, Sticta 15x, Stramonium 15x.

INDICATIONS & USAGE SECTION

Aches - Pains Formulated for symptoms associated with bruises, strains and overexertion such as pain, stiffness and inflammation.